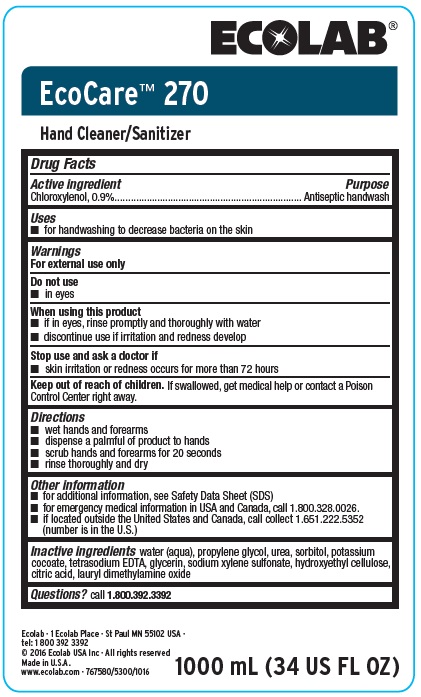 DRUG LABEL: EcoCare 270
NDC: 47593-362 | Form: SOLUTION
Manufacturer: Ecolab Inc.
Category: otc | Type: HUMAN OTC DRUG LABEL
Date: 20240327

ACTIVE INGREDIENTS: CHLOROXYLENOL 9 mg/1 mL
INACTIVE INGREDIENTS: WATER; PROPYLENE GLYCOL; UREA; SORBITOL; POTASSIUM COCOATE; EDETATE SODIUM; GLYCERIN; SODIUM XYLENESULFONATE; HYDROXYETHYL CELLULOSE (3000 CPS AT 1%); ANHYDROUS CITRIC ACID; COCAMINE OXIDE

Drug Facts

Active ingredient

Chloroxylenol, 0.9%

Purpose

Antiseptic Handwash

Uses

- for handwashing to decrease bacteria on the skin

Warnings

For external use only

Do not use

- In eyes

When using this product

- if in eyes, rinse promptly and thoroughly with water
- discontinue use if irritation and redness develop

Stop use and ask doctor if

- skin rritation and redness occurs for more than 72 hours

Keep out of reach of children. If swallowed, get medical help or contact a Poison Control Center right away.

Directions

- wet hands and forearms
- dispense a palmful of product to hands
- scrub hands and forearms for 20 seconds
- rinse thoroughly and dry

Other information

- for additional information, see Safety Data Sheet (SDS)
- for emergency medical information in USA and Canada, call 1.800.328.0026.
- If located outside the United States and Canada, call collect 1.651.222.5352 (number is in the U.S.)

INACTIVE INGREDIENT

Inactive ingredients: water (aqua), propylene glycol, urea, sorbitol, potassium cocoate, tetrasodium EDTA, glycerin, sodium xylene sulfonate, hydroxyethyl cellulose, citric acid, lauryl dimethylamine oxide

QUESTIONS

Qestions? Call 1.800.392.3392

Principal display panel / representative label

EcoCare™ 270

Hand Cleaner/Sanitizer

1000 mL (34 US FL OZ)

Ecolab 1 - Ecolab Place St. Paul MN 55102 USA

tel. 1 800 392 3392

2016® Ecolab USA Inc. - All rights reserved

Made in U.S.A.

www.ecolab.com 767580/5300/1016